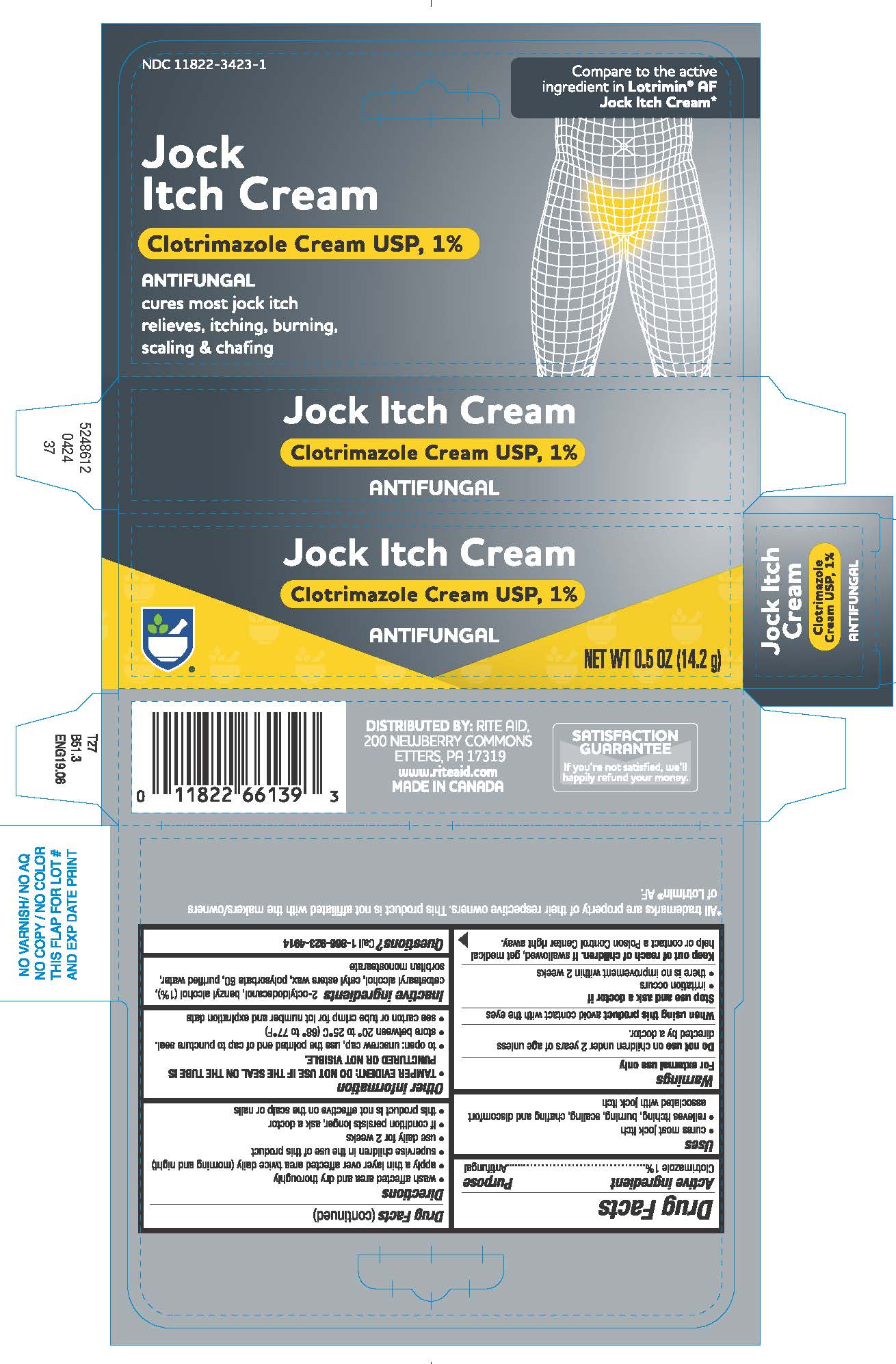 DRUG LABEL: Clotrimazole


NDC: 11822-3423 | Form: CREAM
Manufacturer: Rite Aid Corporation
Category: otc | Type: HUMAN OTC DRUG LABEL
Date: 20250714

ACTIVE INGREDIENTS: CLOTRIMAZOLE 10 mg/1 g
INACTIVE INGREDIENTS: BENZYL ALCOHOL; CETOSTEARYL ALCOHOL; CETYL ESTERS WAX; OCTYLDODECANOL; POLYSORBATE 60; SORBITAN MONOSTEARATE; WATER

Rite Aid
Jock Itch

Drug Facts

Active ingredient

Clotrimazole 1%

Purpose

Antifungal

Uses

- cures most jock itch
- relieves itching, burning, scaling, chafing and discomfort associated with jock itch

Warnings

For external use only

DO NOT USE

Do not useon children under 2 years of age unless directed by a doctor.

When using this productavoid contact with the eyes

Stop use and ask a doctor if

- irritation occurs
- there is no improvement within 2 weeks

Keep out of reach of children.If swallowed, get medical help or contact a Poison Control Center right away.

Directions

- wash affected area and dry thoroughly
- apply a thin layer over affected area twice daily (morning and night)
- supervise children in the use of this product
- use daily for 2 weeks
- if condition persists longer, ask a doctor
- this product is not effective on the scalp or nails

Other information

- TAMPER EVIDENT: DO NOT USE IF THE SEAL ON THE TUBE IS PUNCTURED OR NOT VISIBLE.
- to open: unscrew cap, use the pointed end of cap to puncture seal.
- store between 20° to 25°C (68° to 77°F)
- see carton or tube crimp for lot number and expiration date

Inactive ingredients

2-octyldodecanol, benzyl alcohol (1%), cetostearyl alcohol, cetyl esters wax, polysorbate 60, purified water, sorbitan monostearate

Questions?

Call 1-866-923-4914

DISTRIBUTED BY:
RITE AID, 200 NEWBERRY COMMONS

ETTERS, PA 17319

www.riteaid.com

MADE IN CANADA

PRINCIPAL DISPLAY PANEL - 14.2 g Tube Carton

Jock Itch Cream

Clotrimazole Cream, USP 1%

ANTIFUNGAL

NET WT 0.5 OZ (14.2 g)